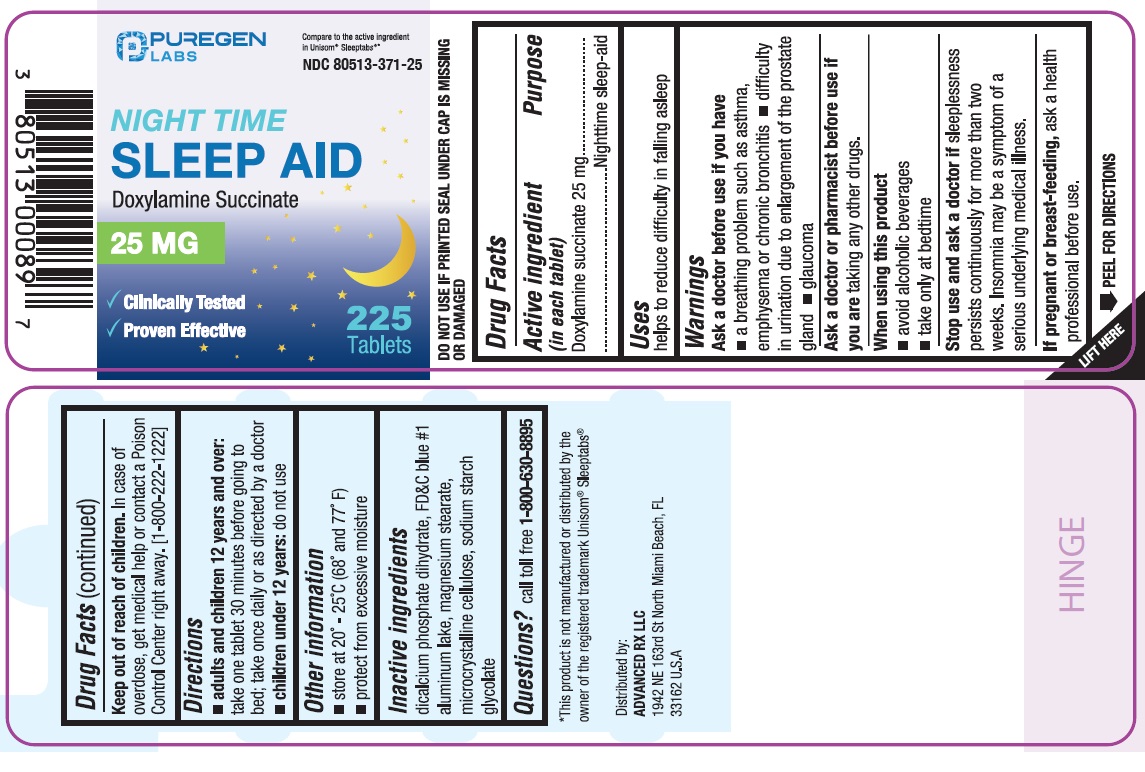 DRUG LABEL: Night Time Sleep Aid
NDC: 80513-371 | Form: TABLET
Manufacturer: Advanced Rx LLC
Category: otc | Type: HUMAN OTC DRUG LABEL
Date: 20250226

ACTIVE INGREDIENTS: DOXYLAMINE SUCCINATE 25 mg/1 1
INACTIVE INGREDIENTS: DIBASIC CALCIUM PHOSPHATE DIHYDRATE; FD&C BLUE NO. 1 ALUMINUM LAKE; MAGNESIUM STEARATE; MICROCRYSTALLINE CELLULOSE; SODIUM STARCH GLYCOLATE TYPE A

Night Time Sleep Aid

Active ingredient (in each tablet)

Doxylamine succinate 25 mg

Purpose

Nighttime sleep-aid

Use

- helps to reduce difficulty in falling asleep

Warnings

Ask a doctor before use if you have

- a breathing problem such as asthma, emphysema or chronic bronchitis
- difficulty in urination due to enlargement of the prostate gland
- glaucoma

Ask a doctor or pharmacist before use if

you are taking any other drugs.

When using this product

- avoid alcoholic beverages
- take only at bedtime

Stop use and ask a doctor if

sleeplessness persists continuously for more than two weeks. Insomnia may be a symptom of serious underlying medical illness.

If pregnant or breast-feeding,

ask a health professional before use.

Keep out of reach of children.

In case of overdose, get medical help or contact a Poison Control Center right away. [1-800-222-1222]

Directions

- adults and children 12 years and over:take one tablet 30 minutes before going to bed; take once daily or as directed by a doctor
- children under 12 years:do not use

Other information

- store at 20°-25°C (68° and 77° F)
- protect from excessive moisture
- DO NOT USE IF PRINTED SEAL UNDER CAP IS MISSING OR DAMAGED.

Inactive ingredients

dicalcium phosphate dihydrate, FD&C blue #1 aluminum lake, magnesium stearate, microcrystalline cellulose, sodium starch glycolate

Questions?

call toll-free 1-800-630-8895

Distributed by:

ADVANCED RX LLC

1942 NE 163rd St North Miami Beach,

FL 33162 U.S.A

PACKAGE LABEL

*Compare to the active ingredient in Unisom®Sleeptabs®

NDC 80513-371-25

Night Time Sleep Aid

Doxylamine Succinate 25 mg

225 Tablets

*This product is not manufactured or distributed by the owner of the registered trademark Unisom®Sleeptabs®.

Good Neighbor 44-386

Good Neighbor 44-386